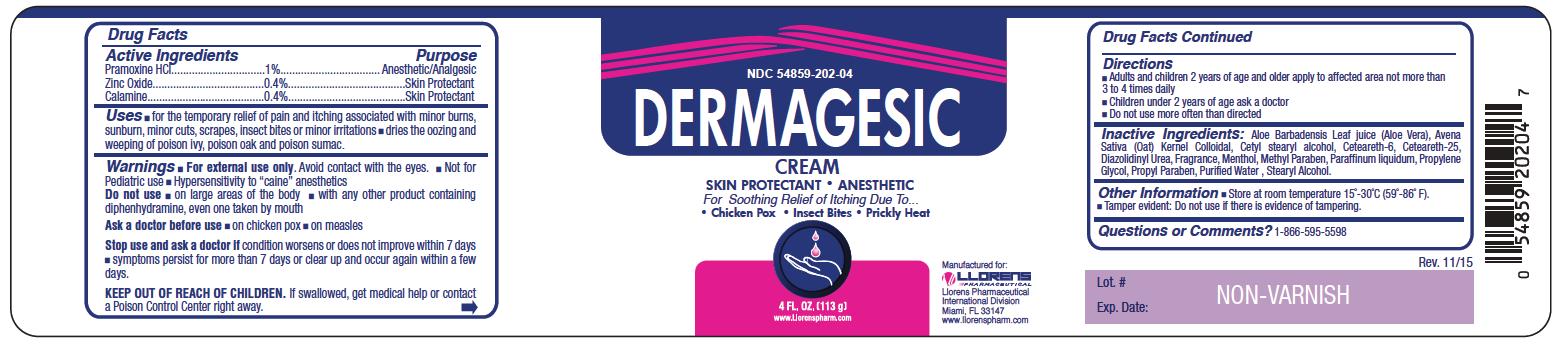 DRUG LABEL: Dermagesic
NDC: 54859-202 | Form: CREAM
Manufacturer: Llorens Pharmaceutical International Division
Category: otc | Type: HUMAN OTC DRUG LABEL
Date: 20251231

ACTIVE INGREDIENTS: PRAMOXINE HYDROCHLORIDE 10 mg/1 g; ZINC OXIDE 4 mg/1 g; FERRIC OXIDE RED 4 mg/1 g
INACTIVE INGREDIENTS: ALOE; AVENA SATIVA WHOLE; CETOSTEARYL ALCOHOL; CETEARETH-6; CETEARETH-25; DIAZOLIDINYL UREA; MENTHOL; METHYLPARABEN; MINERAL OIL; PROPYLENE GLYCOL; PROPYLPARABEN; WATER; STEARYL ALCOHOL

Dermagesic 202

Active Ingredients

Pramoxine HCl 1%

Zinc Oxide 0.4%

Calamine 0.4%

Purpose

Anestheric/Analgesic

Skin Protectant

Uses

- for temporary reilef of pain and itching associated with minor burns, sunburn, minor cuts, scrapes, insect bites or minor irritation
- dries the oozing and weeping of poison ivy, poison oak and poison sumac.

Warnings

For external use only. Avoid contact with the eyes

- Not for Pediatric use
- Hypersensitivity to "caine" anesthetics

Do not use

- on large areas of the body
- with any other product containing diphenhydramine, even one taken by mouth.

Ask a doctor before use

- on chicken pox
- on measles

Stop use and ask a doctor if condition worsens or does not improve within 7 days

- symptoms persist for more than 7 days or clear up and occur again within a few days

Keep out of reach of children. If swallowed, get medical help or contact a Poison Control Center right away.

Directions

- Adults and children 2 years of age and older apply to affected area not more than 3 to 4 times daily
- Children under 2 years of age ask a doctor
- Do not use more often than directed

Inactive Ingredients

Aloe Badbadensis Leaf juice (Aloe Vera), Avena Sativa (Oat) Kernal colloidal, cetyl stearyl alcohol, ceteareth-6, ceteareth-25, diazolidinyl urea, fragrance, menthol, methyl paraben, paraffinum liquidum, propylene glycol, propyl paraben, purified water, stearyl alcohol

Questions or Comments

1-866-595-5598